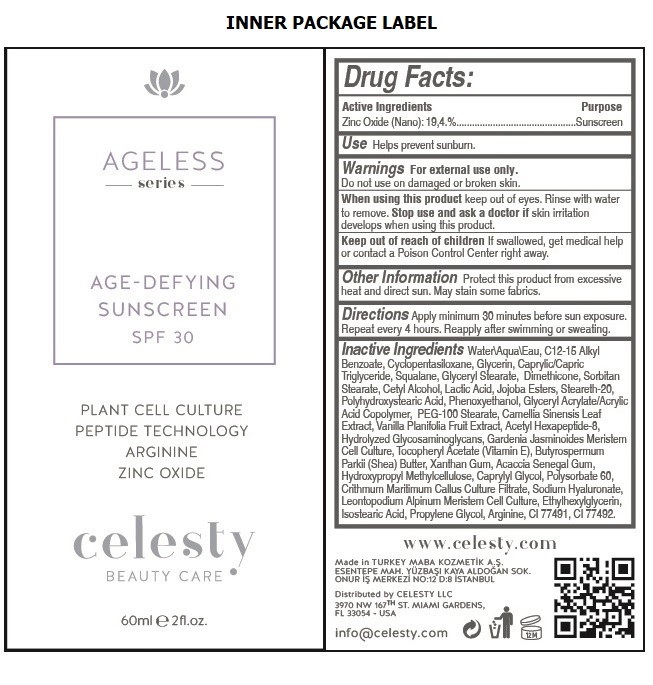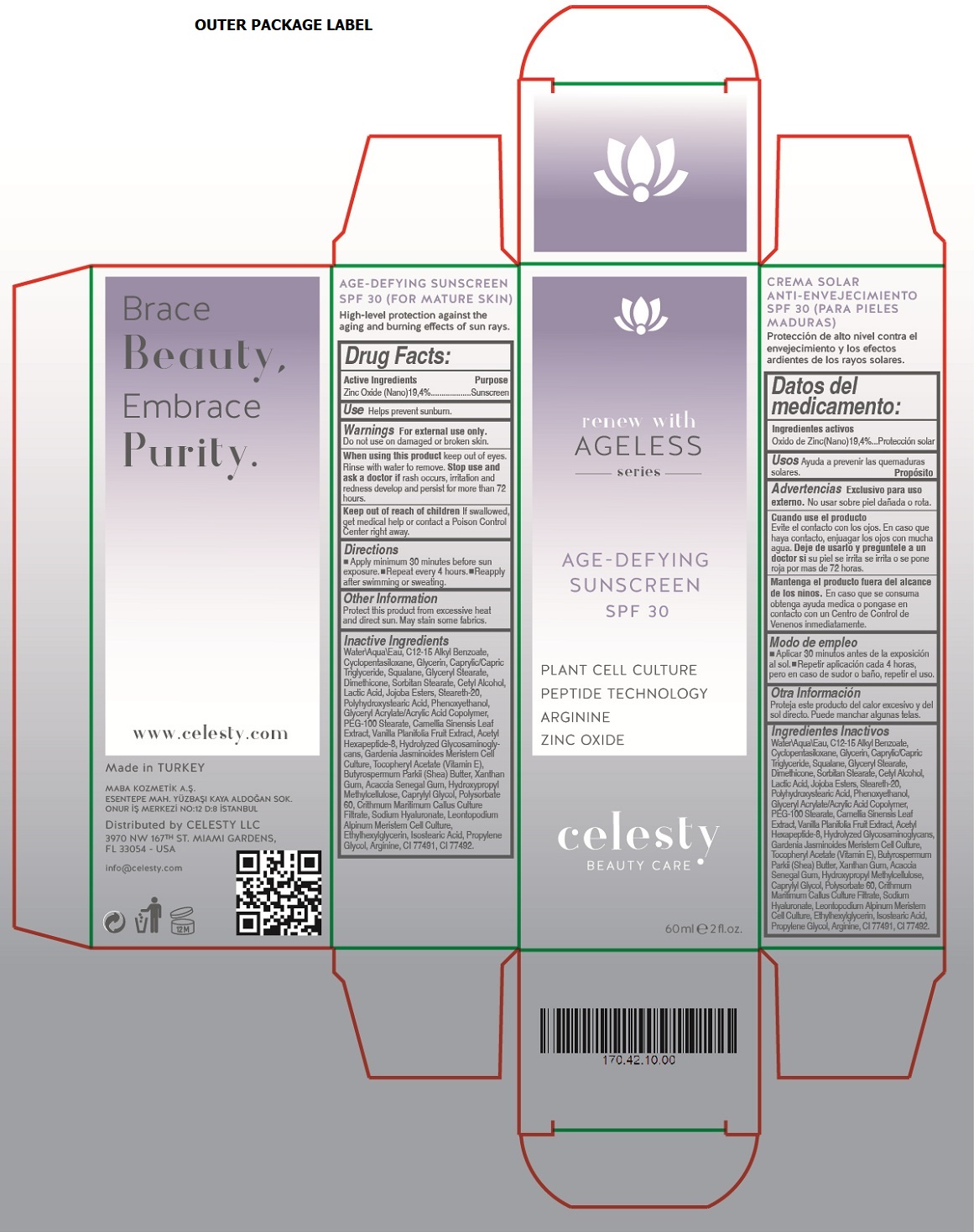 DRUG LABEL: Celesty
NDC: 81120-106 | Form: LOTION
Manufacturer: MABA KOZMETIK LIMITED SIRKETI
Category: otc | Type: HUMAN OTC DRUG LABEL
Date: 20201209

ACTIVE INGREDIENTS: ZINC OXIDE 194 mg/1 mL
INACTIVE INGREDIENTS: WATER; ALKYL (C12-15) BENZOATE; CYCLOMETHICONE 5; GLYCERIN; MEDIUM-CHAIN TRIGLYCERIDES; SQUALANE; GLYCERYL MONOSTEARATE; DIMETHICONE; SORBITAN MONOSTEARATE; CETYL ALCOHOL; LACTIC ACID, UNSPECIFIED FORM; HYDROGENATED JOJOBA OIL, RANDOMIZED; STEARETH-20; POLYHYDROXYSTEARIC ACID (2300 MW); PHENOXYETHANOL; POLYACRYLIC ACID (250000 MW); PEG-100 STEARATE; GREEN TEA LEAF; VANILLA BEAN; ACETYL HEXAPEPTIDE-8; HYDROLYZED GLYCOSAMINOGLYCANS (BOVINE; 50000 MW); GARDENIA JASMINOIDES FRUIT; .ALPHA.-TOCOPHEROL ACETATE; SHEA BUTTER; XANTHAN GUM; ACACIA; HYPROMELLOSE, UNSPECIFIED; CAPRYLYL GLYCOL; POLYSORBATE 60; CRITHMUM MARITIMUM WHOLE; HYALURONATE SODIUM; LEONTOPODIUM NIVALE SUBSP. ALPINUM ROOT; ETHYLHEXYLGLYCERIN; ISOSTEARIC ACID; PROPYLENE GLYCOL; ARGININE; FERRIC OXIDE RED; FERRIC OXIDE YELLOW

celesty AGELESS series AGE - DEFYING SUNSCREEN SPF 30

Active Ingredients

Zinc Oxide (Nano) 19.4%

Purpose

Sunscreen

Use

Helps prevent sunburn.

Warnings

For external use only. Do not use on damaged or broken skin.

When using this product keep out of eyes. Rinse with water to remove. Stop use and ask a doctor if rash occurs, irritation and redness develop and persist for more than 72 hours.

Keep out of reach of children If swallowed, get medical help or contact a Poison Control Center right away.

Directions

• Apply minimum 30 minutes before sun exposure. • Repeat every 4 hours • Reapply after swimming or sweating.

Other Information

Protect this product from excessive heat and direct sun. May stain some fabrics.

Inactive Ingredients

Water\Aqua\Eau, C12-15 Alkyl Benzoate, Cyclopentasiloxane, Glycerin, Caprylic/Capric Triglyceride, Squalane, Glyceryl Stearate, Dimethicone, Sorbitan Stearate, Cetyl Alcohol, Lactic Acid, Jojoba Esters, Steareth-20, Polyhydroxystearic Acid, Phenoxyethanol, Glyceryl Acrylate/Acrylic Acid Copolymer, PEG-100 Stearate, Camellia Sinensis Leaf Extract, Vanilla Planifolia Fruit Extract, Acetyl Hexapeptide-8, Hydrolyzed Glycosaminoglycans, Gardenia Jasminoides Meristem Cell Culture, Tocopheryl Acetate (Vitamin E), Butyrospermum Parkii (Shea) Butter, Xanthan Gum, Acacia Senegal Gum, Hydroxypropyl Methylcellulose, Caprylyl Glycol, Polysorbate 60, Crithmum Maritimum Callus Culture Filtrate, Sodium Hyaluronate, Leontopodium Alpinum Meristem Cell Culture, Ethylhexylglycerin, Isostearic Acid, Propylene Glycol, Arginine, CI 77491, CI 77492

renew with AGELESS series

PLANT CELL CULTURE

PEPTIDE TECHNOLOGY

ARGININE

ZINC OXIDE

BEAUTY CARE

Brace Beauty, Embrace Purity.

www.celesty.com

Made in TURKEY

MABA KOZMETIK A.S.

ESENTEPE MAH. YUZBASI KAYA ALDOGAN SOK.

ONUR IS MERKEZI NO:12 D:8 ISTANBUL

Distributed by CELESTY LLC

3970 NW 167TH ST. MIAMI GARDENS,

FL 33054 - USA

info@celesty.com

(FOR MATURE SKIN)

High-level protection against the aging and burning effects of sun rays.